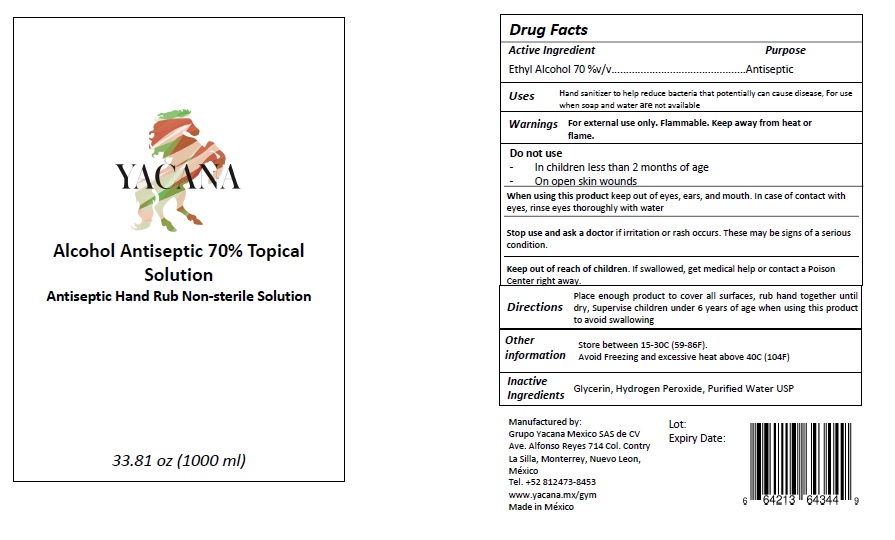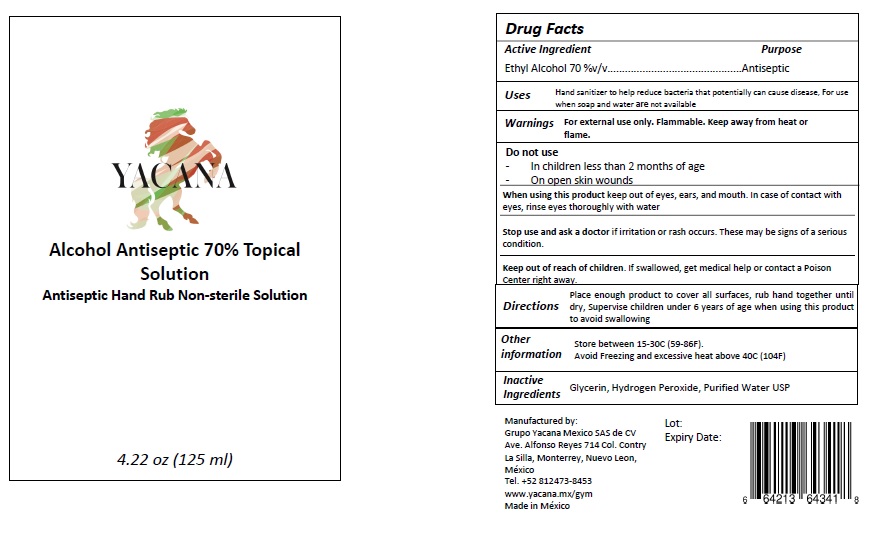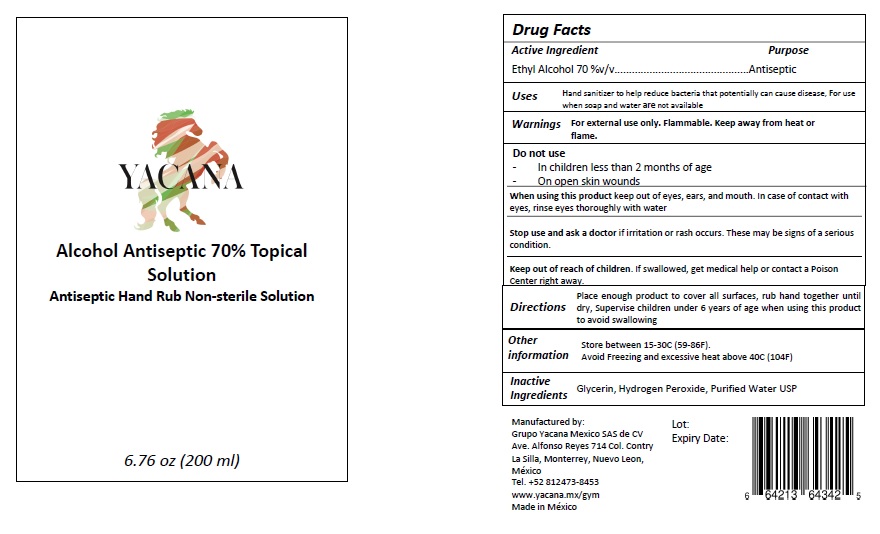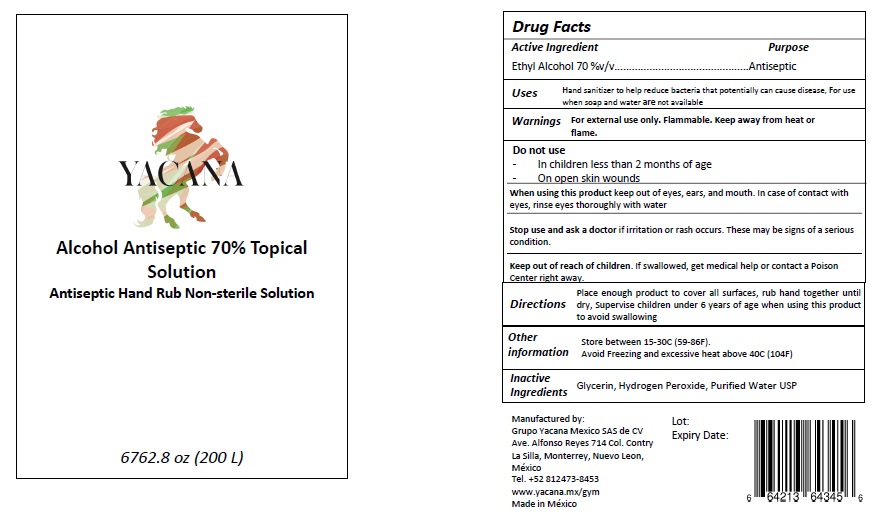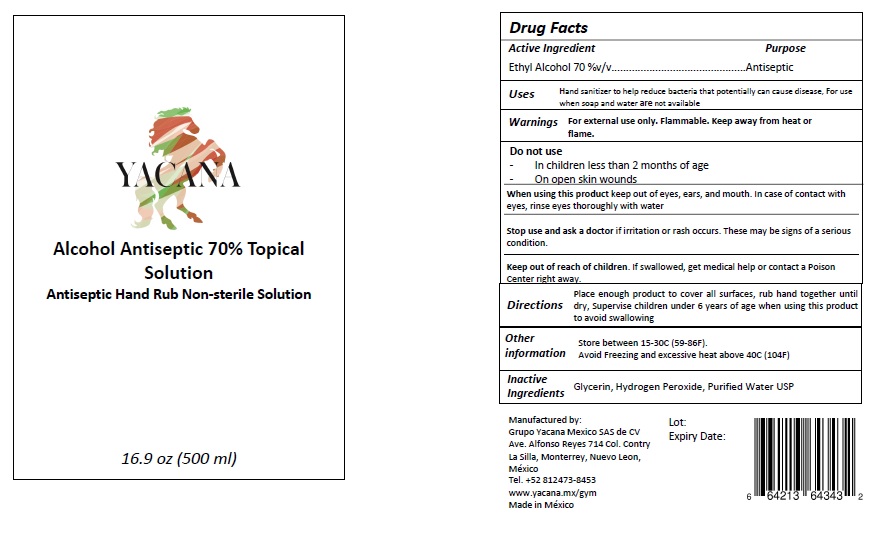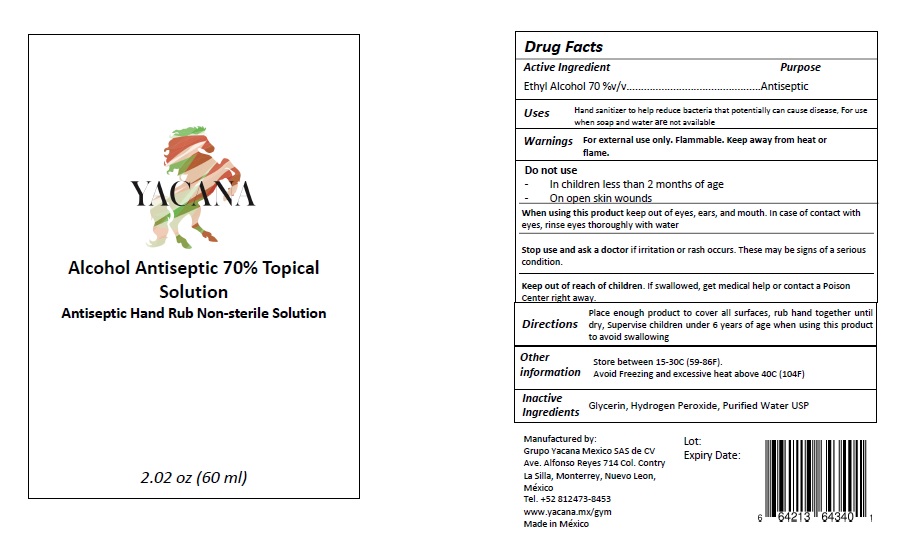 DRUG LABEL: Alcohol Antiseptic 70% Topical Solution
NDC: 76592-002 | Form: GEL
Manufacturer: Grupo Yacana Mexico SAS de CV
Category: otc | Type: HUMAN OTC DRUG LABEL
Date: 20200505

ACTIVE INGREDIENTS: ALCOHOL 70 mL/100 mL
INACTIVE INGREDIENTS: GLYCERIN; HYDROGEN PEROXIDE; WATER

Active Ingredient

Ethyl Alcohol 70% v/v.

Purpose

Antiseptic

Uses

Hand sanitizer to help reduce bacteria that potentially can cause disease. For use when soap and water are not available.

Warnings

For external use only. Flammable. Keep away from heat or flame.

Do not use

- In children less than 2 months of age
- On open skin wounds

When using this product keep out of eyes, ears, and mouth. In case of contact with eyes, rinse eyes thoroughly with water.

Stop use and ask a doctor if irritation or rash occurs. These may be signs of a serious condition.

Keep out of reach of children. If swallowed, get medical help or contact a Poison Center right away.

Directions

Place enough product to cover all surfaces, rub hand together until dry, Supervise children under 6 years of age when using this product
to avoid swallowing.

Other information

Store between 15-30C (59-86F).
Avoid Freezing and excessive heat above 40C (104F)

Inactive ingredients

Glycerin, Hydrogen Peroxide, Purified Water USP